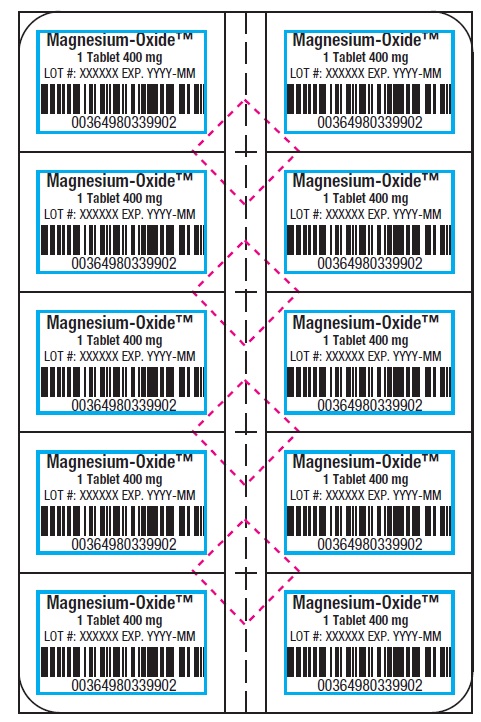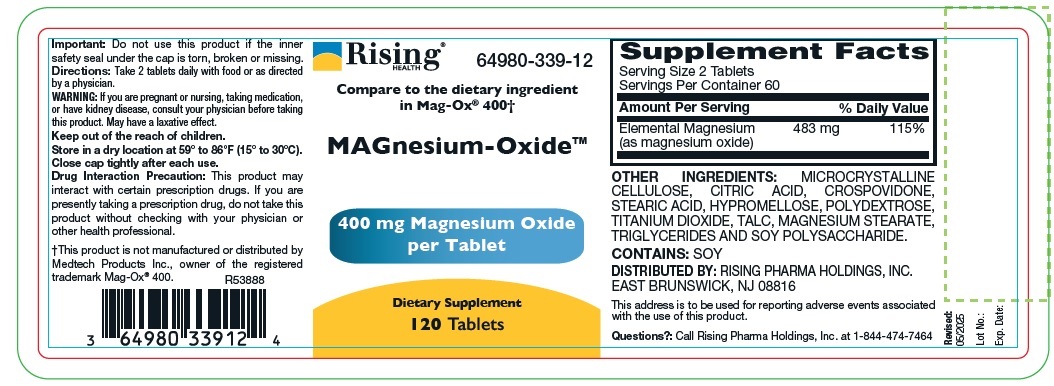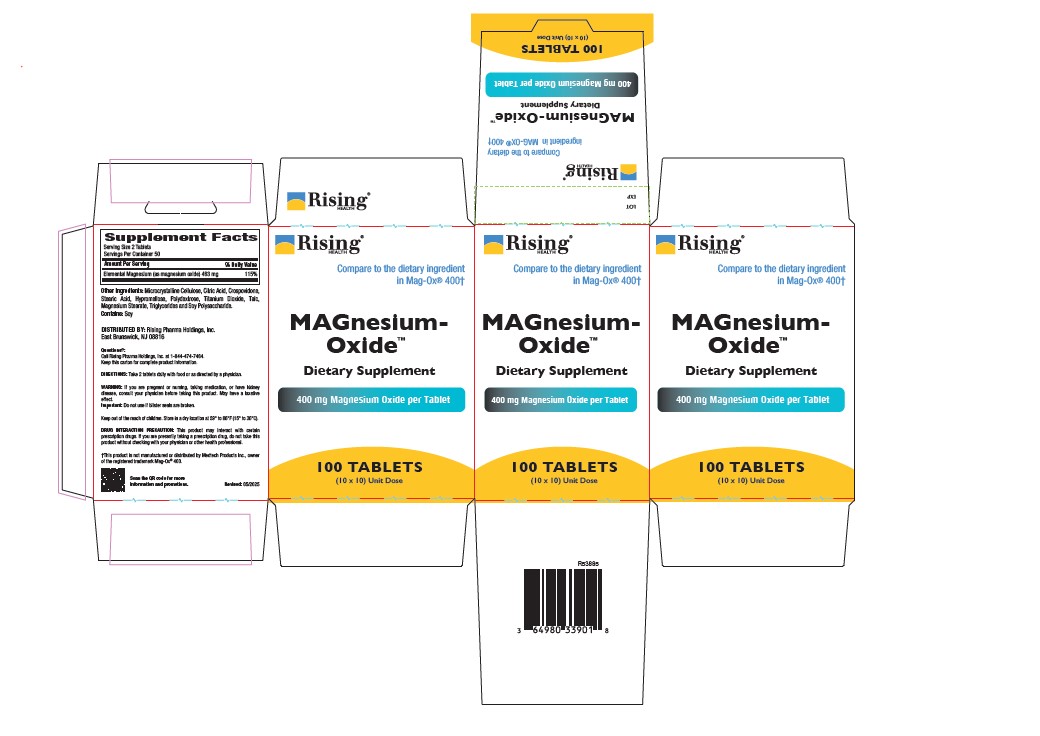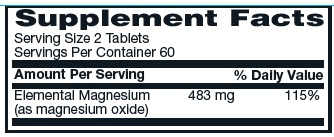 DRUG LABEL: Magnesium Oxide
NDC: 64980-339 | Form: TABLET
Manufacturer: Rising Pharma Holdings, Inc.
Category: other | Type: DIETARY SUPPLEMENT
Date: 20250624

ACTIVE INGREDIENTS: MAGNESIUM OXIDE 483 mg/1 1
INACTIVE INGREDIENTS: Microcrystalline Cellulose; CITRIC ACID; CROSPOVIDONE; STEARIC ACID; HYPROMELLOSE, UNSPECIFIED; POLYDEXTROSE; TITANIUM DIOXIDE; TALC; Magnesium Stearate; C18-36 ACID TRIGLYCERIDE; PEG-5 SOY STEROL

MAGnesium-Oxide, Dietary Supplement, 120 Tablets

HEALTH CLAIM

OTHER INGREDIENTS: MICROCRYSTALLINE CELLULOSE, CITRIC ACID, CROSPOVIDONE, STEARIC ACID, HYPROMELLOSE, POLYDEXTROSE,
TITANIUM DIOXIDE, TALC, MAGNESIUM STEARATE, TRIGLYCERIDES AND SOY POLYSACCHARIDE.
CONTAINS: SOY

DOSAGE AND ADMINISTRATION

Important: Do not use this product if the inner safety seal under the cap is torn, broken or missing.

Directions: Take 2 tablets daily with food or as directed by a physician.

WARNING

If you are pregnant or nursing, taking medication, or have kidney disease, consult your physician before taking this product. May have a laxative effect.

Keep out of the reach of children.

SAFE HANDLING WARNING

Store in a dry location at 59° to 86°F (15° to 30°C).

Close cap tightly after each use.

PRECAUTIONS

Drug Interaction Precaution: This product may interact with certain prescription drugs. If you are presently taking a prescription drug, do not take this product without checking with your physician or other health professional.

†This product is not manufactured or distributed by Medtech Products Inc., owner of the registered trademark Mag-Ox® 400.

R53888

DISTRIBUTED BY: RISING PHARMA HOLDINGS, INC. EAST BRUNSWICK, NJ 08816

This address is to be used for reporting adverse events associated with the use of this product.
Questions?: Call Rising Pharma Holdings, Inc. at 1-844-474-7464

Revised:06/2025

Lot No.:

Exp. Date:

PACKAGE LABEL.PRINCIPAL DISPLAY PANEL

MAGnesium-Oxide™

Dietary Supplement

120 Tablets

Bottle Label (64980-339-12)

MAGnesium-Oxide™

Dietary Supplement

100 TABLETS (10 x 10) Unit Dose

Carton Label (64980-339-01)

MAGnesium-Oxide™

Dietary Supplement

10 TABLETS (in 1 Blister)

Blister Label (64980-339-90)